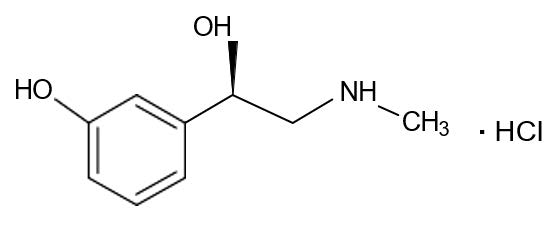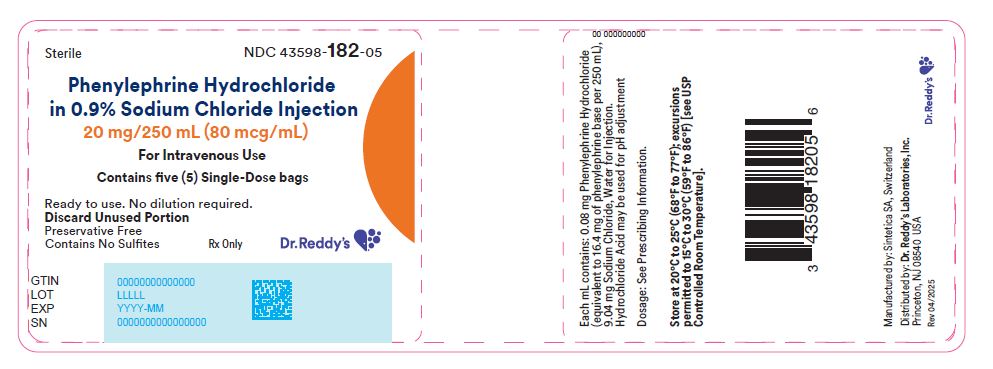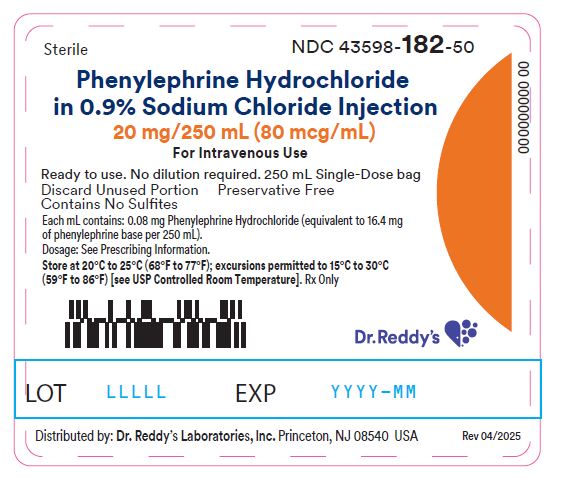 DRUG LABEL: phenylephrine hydrochloride injection, solution
NDC: 43598-182 | Form: INJECTION, SOLUTION
Manufacturer: Dr. Reddy's Laboratories Inc.
Category: prescription | Type: HUMAN PRESCRIPTION DRUG LABEL
Date: 20251223

ACTIVE INGREDIENTS: PHENYLEPHRINE 80 ug/1 mL
INACTIVE INGREDIENTS: SODIUM CHLORIDE; HYDROCHLORIC ACID; WATER; NITROGEN

HIGHLIGHTS OF PRESCRIBING INFORMATION

These highlights do not include all the information needed to use Phenylephrine Hydrochloride in 0.9% Sodium Chloride Injection safely and effectively. See full prescribing information for Phenylephrine Hydrochloride Injection.
PHENYLEPHRINE HYDROCHLORIDE IN SODIUM CHLORIDE injection, for intravenous use
Initial U.S. Approval: 2012

1 INDICATIONS AND USAGE

Phenylephrine Hydrochloride in 0.9% Sodium Chloride Injection is an alpha-1 adrenergic receptor agonist indicated for increasing blood pressure in adults with clinically important hypotension resulting primarily from vasodilation, in the setting of anesthesia (1)

2 DOSAGE AND ADMINISTRATION

Do NOT dilute prior to administration (2.1)
Dosing for Perioperative Hypotension

- Intravenous bolus administration: 50 mcg to 250 mcg (2.2)
- Intravenous continuous infusion: 0.5 mcg/kg/minute to 1.4 mcg/kg/minute titrated to effect (2.2)

3 DOSAGE FORMS AND STRENGTHS

njection: 20 mg in 250 mL (80 mcg/mL) of phenylephrine hydrochloride (equivalent to 16.4 mg of phenylephrine base per 250 mL) in 0.9% Sodium Chloride, supplied in a ready-to-use, single-dose intravenous solution bag (3, 11, 16)

4 CONTRAINDICATIONS

- Hypersensitivity to it or any of its components (4)

5 WARNINGS AND PRECAUTIONS

- Severe bradycardia and decreased cardiac output (5.2)
- Extravasation: during intravenous administration may cause necrosis or sloughing of tissue (5.4)
- Concomitant use with oxytocic drugs: pressor effect of sympathomimetic pressor amines is potentiated (5.5)

6 ADVERSE REACTIONS

Most common adverse reactions: nausea and vomiting, headache, nervousness (6)

To report SUSPECTED ADVERSE REACTIONS, contact Dr. Reddy’s Laboratories Inc., at 1-888-375-3784 or FDA at 1-800-FDA-1088 or www.fda.gov/medwatch.

7 DRUG INTERACTIONS

- Agonistic effects with monoamine oxidase inhibitors (MAOI), β-adrenergic blocking agents, α-2 adrenergic agonists, steroids, tricyclic antidepressants, norepinephrine transport inhibitors, ergot alkaloids, centrally-acting sympatholytic agents and atropine sulfate (7.1)
- Antagonistic effects on and by α-adrenergic blocking agents (7.2)

FULL PRESCRIBING INFORMATION

1 INDICATIONS AND USAGE

Phenylephrine Hydrochloride in 0.9% Sodium Chloride Injection is indicated for increasing blood pressure in adults with clinically important hypotension resulting primarily from vasodilation in the setting of anesthesia.

2 DOSAGE AND ADMINISTRATION

2.1 General Administration Instructions

During Phenylephrine Hydrochloride in 0.9% Sodium Chloride Injection, 80 mcg/mL (20 mg/250 mL) administration:

- Correct intravascular volume depletion.
- Correct acidosis. Acidosis may reduce the effectiveness of phenylephrine

Phenylephrine Hydrochloride in 0.9% Sodium Chloride Injection, 80 mcg/mL (20 mg/250 mL) is supplied as a premixed, ready to administer product that requires no further dilution prior to infusion.

Parenteral drug products should be inspected for particulate matter and discoloration prior to administration. Do not use if the solution is coloured or cloudy, or if it contains particulate matter.

Discard any unused portion.

2.2 Recommended Dosage

In adult patients undergoing surgical procedures with either neuraxial anesthesia or general anesthesia:

- 50 mcg to 250 mcg by intravenous bolus administration. The most frequently reported initial bolus dose is 50 mcg or 100 mcg.
- 0.5 mcg/kg/min to 1.4 mcg/kg/min by intravenous continuous infusion, titrated to blood pressure goal. Do not exceed 200 mcg/min.

3 DOSAGE FORMS AND STRENGTHS

Injection: 20 mg in 250 mL (80 mcg/mL) of phenylephrine hydrochloride in 0.9% Sodium Chloride, supplied as a ready-to-use, clear, colorless solution in a single-dose 250-mL intravenous solution bag.

4 CONTRAINDICATIONS

The use of Phenylephrine Hydrochloride Injection, 80 mcg/mL is contraindicated in patients with:

- Hypersensitivity to the product or any of its components

5 WARNINGS AND PRECAUTIONS

5.1 Exacerbation of Angina, Heart Failure, or Pulmonary Arterial Hypertension

Because of its pressor effects, phenylephrine hydrochloride can precipitate angina in patients with severe arteriosclerosis or history of angina, exacerbate underlying heart failure, and increase pulmonary arterial pressure.

5.2 Bradycardia

Phenylephrine hydrochloride can cause severe bradycardia and decreased cardiac output.

5.3 Risk in Patients with Autonomic Dysfunction

The pressor response to adrenergic drugs, including phenylephrine, can be increased in patients with autonomic dysfunction, as may occur with spinal cord injuries.

5.4 Skin and Subcutaneous Necrosis

Extravasation of phenylephrine can cause necrosis or sloughing of tissue. Avoid extravasation by checking infusion site for free flow.

5.5 Pressor Effect with Concomitant Oxytocic Drugs

Oxytocic drugs potentiate the pressor effect of sympathomimetic pressor amines including phenylephrine hydrochloride [see Drug Interactions (7.1)], with the potential for hemorrhagic stroke.

5.6 Peripheral and Visceral Ischemia

Phenylephrine hydrochloride can cause excessive peripheral and visceral vasoconstriction and ischemia to vital organs, particularly in patients with extensive peripheral vascular disease.

5.7 Renal Toxicity

Phenylephrine hydrochloride can increase the need for renal replacement therapy in patients with septic shock. Monitor renal function.

6 ADVERSE REACTIONS

The following adverse reactions associated with the use of phenylephrine hydrochloride were identified in the literature. Because these reactions are reported voluntarily from a population of uncertain size, it is not always possible to estimate their frequency reliably or to establish a causal relationship to drug exposure.

Cardiac disorders: Bradycardia, AV block, ventricular extrasystoles, myocardial ischemia

Gastrointestinal disorders: Nausea, vomiting

General disorders and administrative site conditions: Chest pain, extravasation

Nervous system disorders: Headache, nervousness, paresthesia, tremor

Psychiatric disorders: Excitability

Respiratory: Pulmonary edema, rales

Skin and subcutaneous tissue disorders: Diaphoresis, pallor, piloerection, skin blanching, skin necrosis with extravasation

Vascular disorders: Hypertensive crisis

7 DRUG INTERACTIONS

7.1 Agonists

The pressor effect of phenylephrine hydrochloride is increased in patients receiving:

- Monoamine oxidase inhibitors (MAOI), such as selegiline.
- Oxytocin and oxytocic drugs
- β-adrenergic blockers
- α-2 adrenergic agonists, such as clonidine
- Steroids
- Tricyclic antidepressants
- Norepinephrine transport inhibitors, such as atomoxetine
- Ergot alkaloids, such as methylergonovine maleate
- Centrally-acting sympatholytic agents, such as guanfacine or reserpine
- Atropine sulfate

7.2 Antagonists

α-adrenergic blocking agents, including phenothiazines (e.g., chlorpromazine) and amiodarone block phenylephrine and are in turn blocked by phenylephrine.

8 USE IN SPECIFIC POPULATIONS

8.1 Pregnancy

Risk Summary

Data from randomized controlled trials and meta-analyses with phenylephrine hydrochloride injection use in pregnant women during caesarean section have not established a drug-associated risk of major birth defects and miscarriage. These studies have not identified an adverse effect on maternal outcomes or infant Apgar scores [see Data]. There are no data on the use of phenylephrine during the first or second trimester. In animal reproduction and development studies in normotensive animals, evidence of fetal malformations was noted when phenylephrine was administered during organogenesis via a 1-hour infusion at 1.2 times a human daily dose (HDD) of 10 mg/60 kg/day. Decreased pup weights were noted in offspring of pregnant rats treated with 2.9 times the HDD [See Data].

The estimated background risk of major birth defects and miscarriage for the indicated population is unknown. All pregnancies have a background risk of birth defect, loss, or other adverse outcomes. In the U.S. general population, the estimated background risk of major birth defects and miscarriage in clinically recognized pregnancies is 2-4% and 15-20%, respectively.

Clinical Considerations

Disease-Associated Maternal and/or Embryofetal Risk

Untreated hypotension associated with spinal anesthesia for cesarean section is associated with an increase in maternal nausea and vomiting. A sustained decrease in uterine blood flow due to maternal hypotension may result in fetal bradycardia and acidosis.

Data

Human Data

Published randomized controlled trials over several decades, which compared the use of phenylephrine injection to other similar agents in pregnant women during cesarean section, have not identified adverse maternal or infant outcomes. At recommended doses, phenylephrine does not appear to affect fetal heart rate or fetal heart variability to a significant degree.

There are no studies on the safety of phenylephrine injection exposure during the period of organogenesis, and therefore, it is not possible to draw any conclusions on the risk of birth defects following exposure to phenylephrine injection during pregnancy. In addition, there are no data on the risk of miscarriage following fetal exposure to phenylephrine injection.

Animal Data

No clear malformations or fetal toxicity were reported when normotensive pregnant rabbits were treated with phenylephrine via continuous intravenous infusion over 1 hour (0.5 mg/kg/day; approximately equivalent to a HDD based on body surface area) from Gestation Day 7 to 19. At this dose, which demonstrated no maternal toxicity, there was evidence of developmental delay (altered ossification of sternebra).

In a non-GLP dose range-finding study in normotensive pregnant rabbits, fetal lethality and cranial, paw, and limb malformations were noted following treatment with 1.2 mg/kg/day of phenylephrine via continuous intravenous infusion over 1 hour (2.3-times the HDD). This dose was clearly maternally toxic (increased mortality and significant body weight loss). An increase in the incidence of limb malformation (hyperextension of the forepaw) coincident with high fetal mortality was noted in a single litter at 0.6 mg/kg/day (1.2-times the HDD) in the absence of maternal toxicity.

No malformations or embryo-fetal toxicity were reported when normotensive pregnant rats were treated with up to 3 mg/kg/day phenylephrine via continuous intravenous infusion over 1 hour (2.9-times the HDD) from Gestation Day 6 to 17. This dose was associated with some maternal toxicity (decreased food consumption and body weights).

Decreased pup weights were reported in a pre- and postnatal development toxicity study in which normotensive pregnant rats were administered phenylephrine via continuous intravenous infusion over 1 hour (0.3, 1.0, or 3.0 mg/kg/day; 0.29, 1, or 2.9 times the HDD) from Gestation Day 6 through Lactation Day 21). No adverse effects on growth and development (learning and memory, sexual development, and fertility) were noted in the offspring of pregnant rats at any dose tested. Maternal toxicities (mortality late in gestation and during lactation period, decreased food consumption and body weight) occurred at 1 and 3 mg/kg/day of phenylephrine (equivalent to and 2.9 times the HDD, respectively).

8.2 Lactation

Risk Summary

There are no data on the presence of Phenylephrine Hydrochloride Injection or its metabolite in human or animal milk, the effects on the breastfed infant, or the effects on milk production. The developmental and health benefits of breastfeeding should be considered along with the mother’s clinical need for phenylephrine hydrochloride injection and any potential adverse effects on the breastfed infant from phenylephrine hydrochloride injection or from the underlying maternal condition.

8.4 Pediatric Use

Safety and effectiveness in pediatric patients have not been established.

8.5 Geriatric Use

Clinical studies of phenylephrine did not include sufficient numbers of subjects aged 65 and over to determine whether they respond differently from younger subjects. Other reported clinical experience has not identified differences in responses between the elderly and younger patients. In general, dose selection for an elderly patient should be cautious, usually starting at the low end of the dosing range, reflecting the greater frequency of decreased hepatic, renal, or cardiac function, and of concomitant disease or other drug therapy.

8.6 Hepatic Impairment

In patients with liver cirrhosis [Child Pugh Class A (n=3), Class B (n=5) and Class C (n=1)], dose-response data indicate decreased responsiveness to phenylephrine. Consider using larger doses than usual in hepatic impaired subjects.

8.7 Renal Impairment

In patients with end stage renal disease (ESRD) undergoing hemodialysis, dose-response data indicates increased responsiveness to phenylephrine. Consider using lower doses of phenylephrine hydrochloride in ESRD patients.

10 OVERDOSAGE

Overdose of Phenylephrine Hydrochloride Injection, 80 mcg/mL (20 mg/250 mL) can cause a rapid rise in blood pressure. Symptoms of overdose include headache, vomiting, hypertension, reflex bradycardia, and cardiac arrhythmias including ventricular extrasystoles and ventricular tachycardia, and may cause a sensation of fullness in the head and tingling of the extremities.

Consider using an α-adrenergic antagonist.

11 DESCRIPTION

Phenylephrine Hydrochloride in 0.9% Sodium Chloride Injection, 80 mcg/mL (20 mg/250 mL), an alpha-1 adrenergic receptor agonist, contains the active pharmaceutical ingredient phenylephrine in the form of hydrochloride salt. Phenylephrine is a synthetic sympathomimetic agent in sterile form for parenteral injection. Phenylephrine hydrochloride chemical name is (-)-m-Hydroxy-α-[(methylamino) methyl]benzyl alcohol hydrochloride and has the following structural formula:

Phenylephrine hydrochloride is very soluble in water, freely soluble in ethanol, and insoluble in chloroform and ethyl ether. Phenylephrine hydrochloride is sensitive to light.

Phenylephrine Hydrochloride Injection, USP 80 mcg/mL (20 mg/250 mL, equivalent to 16.4 mg of phenylephrine base per 250 ml) is a clear and colorless sterile aqueous solution, essentially free of visible foreign matter. It is a ready-to-use solution intended for intravenous administration.

Each mL contains: 0.08 mg of Phenylephrine Hydrochloride and 9.04 mg of Sodium Chloride in Water for Injection. Phenylephrine Hydrochloride Injection, USP 80 mcg/mL. Hydrochloric acid is added as needed to adjust pH (pH range is 3.0 to 5.0).

12 CLINICAL PHARMACOLOGY

12.1 Mechanism of Action

Phenylephrine hydrochloride is an α-1 adrenergic receptor agonist.

12.2 Pharmacodynamics

Phenylephrine is the active moiety. Metabolites are inactive at both the α-1 and α-2 adrenergic receptors. Following parenteral administration of phenylephrine hydrochloride, increases in systolic blood pressure, diastolic blood pressure, mean arterial blood pressure, and total peripheral vascular resistance are observed. The onset of blood pressure increase following an intravenous bolus phenylephrine hydrochloride administration is rapid and the effect may persist for up to 20 minutes. As mean arterial pressure increases following parenteral doses, vagal activity also increases, resulting in reflex bradycardia.

Most vascular beds are constricted, including renal, splanchnic, and hepatic.

12.3 Pharmacokinetics

Following an intravenous infusion of phenylephrine hydrochloride, the effective half-life was approximately 5 minutes. The steady-state volume of distribution (340 L) exceeded the body volume by a factor of 5, suggesting a high distribution into certain organ compartments. The average total serum clearance (2095 mL/min) was close to one-third of the cardiac output.

A mass balance study showed that phenylephrine is extensively metabolized by the liver with only 12% of the dose excreted unchanged in the urine. Deamination by monoamino oxidase is the primary metabolic pathway resulting in the formation of the major metabolite (m-hydroxymandelic acid) which accounts for 57% of the total administered dose.

13 NONCLINICAL TOXICOLOGY

13.1 Carcinogenesis, Mutagenesis, Impairment Of Fertility

Carcinogenesis:

Long-term animal studies that evaluated the carcinogenic potential of orally administered phenylephrine hydrochloride in F344/N rats and B6C3F1 mice were completed by the National Toxicology Program using the dietary route of administration. There was no evidence of carcinogenicity in mice administered approximately 270 mg/kg/day (131-times the human daily dose (HDD) of 10 mg/day based on body surface area) or rats administered approximately 50 mg/kg/day (48-times the HDD based on body surface area comparisons).

Mutagenesis:

Phenylephrine hydrochloride tested negative in the in vitro bacterial reverse mutation assay (S. typhimurium strains TA98, TA100, TA1535 and TA1537), the in vitro chromosomal aberrations assay, the in vitro sister chromatid exchange assay, and the in vivo rat micronucleus assay. Positive results were reported in only one of two replicates of the in vitro mouse lymphoma assay.

Impairment of Fertility:

No adverse effects on fertility or early embryonic development were noted when phenylephrine hydrochloride was administered at doses of 50 mcg, 100 mcg, or 200 mcg/kg/day (up to 0.2 times HDD of 10 mg/60 kg/day based on body surface area) via single daily bolus injection for 28 days prior to mating to male rats or for 14 days prior to mating through Gestation Day 7 to female rats.

14 CLINICAL STUDIES

Increases in systolic and mean blood pressure following administration of phenylephrine were observed in 42 literature-based studies in the perioperative setting, including 26 studies where phenylephrine was used in lowrisk (ASA 1 and 2) pregnant women undergoing neuraxial anesthesia during cesarean delivery, 3 studies in non-obstetric surgery under neuraxial anesthesia, and 13 studies in patients undergoing surgery under general anesthesia.

16 HOW SUPPLIED/STORAGE AND HANDLING

Phenylephrine Hydrochloride in 0.9% Sodium Chloride Injection is a clear, colorless solution supplied in a readyto- use single dose 250 mL infusion bag as follows:

Unit of Sale | Strength | Each
NDC 43598-182-05 Pack of 5 intravenous solution bags in a cardboard box (20 mg/250 mL) | 80 mcg/mL | NDC 43598-182-50 250 mL intravenous solution bag

Store at 20°C to 25°C (68°F to 77°F), excursions permitted to 15°C to 30°C (59°F to 86°F) [See USP Controlled Room Temperature].

Discard any unused portion.

Manufactured by: Sintetica SA, Switzerland

Distributed by: Dr. Reddy’s Laboratories Inc.,
Princeton, NJ 08540 USA

Principle Display Panel

Phenylephrine Hydrochloride Injection, 20 mg/250 mL (80 mcg/mL) Carton Label

Phenylephrine Hydrochloride Injection, 20 mg/250 mL (80 mcg/mL) Container Label